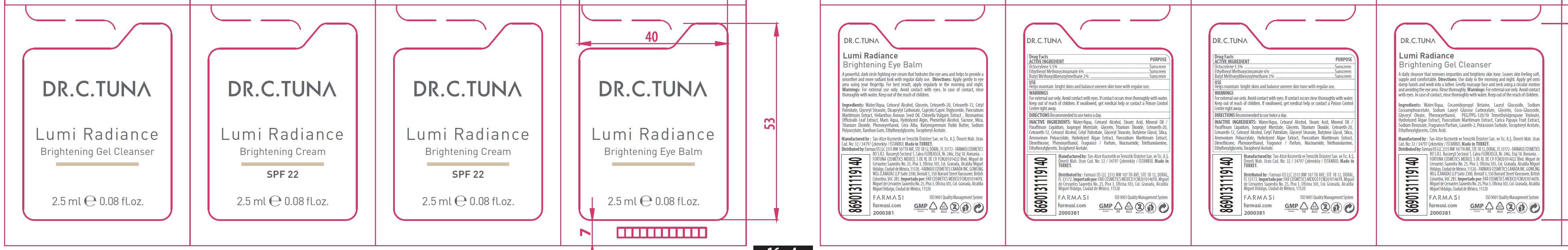 DRUG LABEL: Dr. C. Tuna Lumi Radiance Brightening Cream 22 SPF
NDC: 74690-023 | Form: KIT | Route: TOPICAL
Manufacturer: Farmasi US LLC
Category: otc | Type: HUMAN OTC DRUG LABEL
Date: 20231105

ACTIVE INGREDIENTS: OCTOCRYLENE 55 mg/1 mL; OCTINOXATE 60 mg/1 mL; AVOBENZONE 20 mg/1 mL
INACTIVE INGREDIENTS: WATER; CETOSTEARYL ALCOHOL; STEARIC ACID; MINERAL OIL; ISOPROPYL MYRISTATE; GLYCERIN; TITANIUM DIOXIDE; POLYOXYL 20 CETOSTEARYL ETHER; CETEARETH-12; CETYL PALMITATE; GLYCERYL MONOSTEARATE; BUTYLENE GLYCOL; SILICON DIOXIDE; DIMETHICONE; PHENOXYETHANOL; NIACINAMIDE; TROLAMINE; ETHYLHEXYLGLYCERIN; .ALPHA.-TOCOPHEROL ACETATE

Dr. C. Tuna Lumi Radiance Brightening Cream 22 SPF

ACTIVE INGREDIENT

Octocrylene 5.5%

Ethylhexyl Methoxycinnamate 6%

Butyl Methoxydibenzoylmethane 2%

PURPOSE

Sunscreen

USE

Helps maintain bright skins and balance uneven skin tone with regular use.

WARNINGS

For external use only. Avoid contact with eyes. If contact occurs rinse thoroughly with water.

Keep out of reach of children.

If swallowed, get medical help or contact a Poison Control Center right away.

DIRECTIONS

Recommended to use twice a day.

INACTIVE INGREDIENTS:

Water/Aqua, Cetearyl Alcohol, Stearic Acid, Mineral Oil / Paraffinum Liquidum, Isopropyl Myristate, Glycerin, Titanium Dioxide, Ceteareth-20, Ceteareth-12, Cetearyl Alcohol, Cetyl Palmitate, Glyceryl Stearate, Butylene Glycol, Silica, Ammonium Polyacrylate, Hydrolyzed Algae Extract, Pancratium Maritimum Extract, Dimethicone, Phenoxyethanol, Fragrance / Parfum, Niacinamide, Triethanolamine, Ethylhexylglycerin, Tocopheryl Acetate.